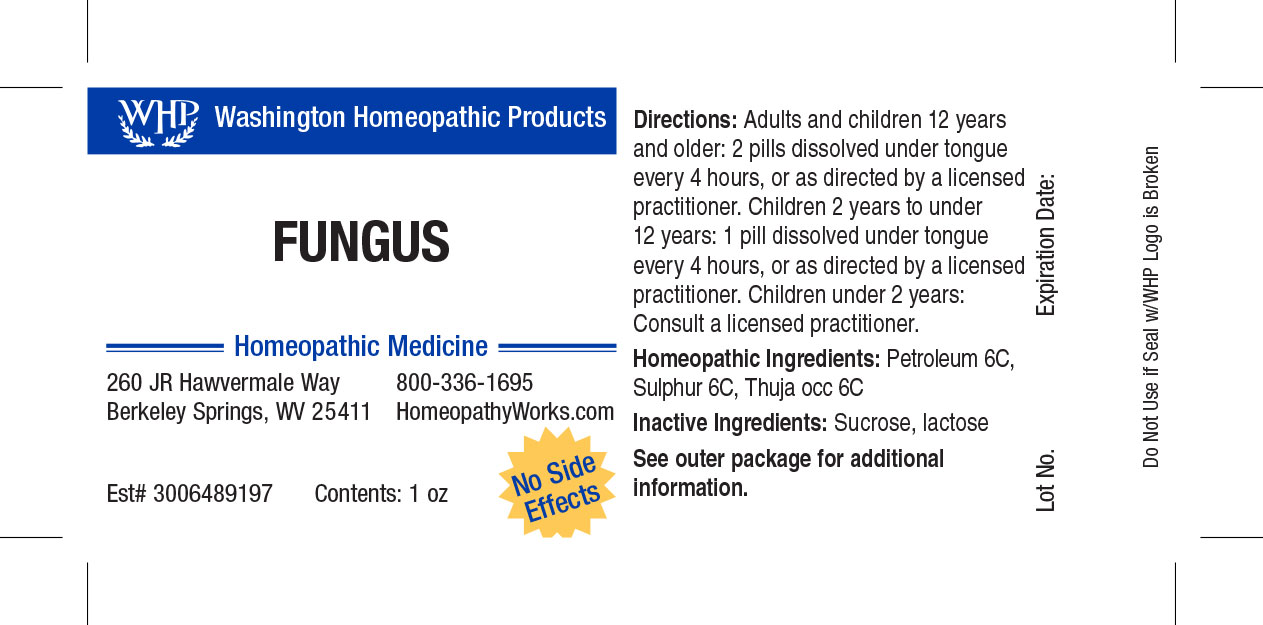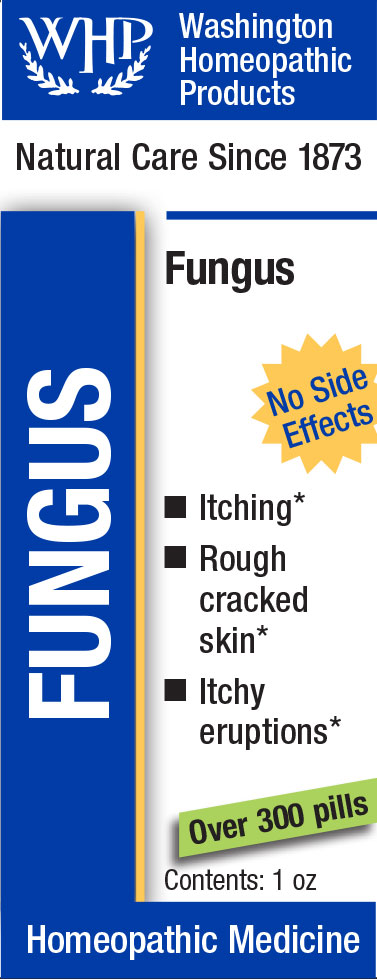 DRUG LABEL: WHP Fungus
NDC: 71919-806 | Form: PELLET
Manufacturer: Washington Homeopathic Products
Category: homeopathic | Type: HUMAN OTC DRUG LABEL
Date: 20250128

ACTIVE INGREDIENTS: THUJA OCCIDENTALIS LEAFY TWIG 6 [hp_C]/1 1; KEROSENE 6 [hp_C]/1 1; SULFUR 6 [hp_C]/1 1
INACTIVE INGREDIENTS: SUCROSE; LACTOSE

ACTIVE INGREDIENTS

PETROLEUM 6C

SULPHUR 6C

THUJA OCC 6C

USES

Temporarily relieves itching eruptions of the skin, as in ringworm or athlete's foot.

KEEP OUT OF REACH OF CHILDREN

As with all medications, keep out of reach of children.

INDICATIONS

PETROLEUM Nausea

SULPHUR Skin problems

THUJA OCC Warts

STOP USE AND ASK DOCTOR

If symptoms persist or recur, discontinue use. If pregnant or nursing, consult a licensed practitioner before using this product.

DIRECTIONS

Directions: Adults and children 12 years and older: 2 pills dissolved under tongue every 4 hours, or as directed by a licensed practitioner. Children 4 years to under 12 years: 1 pill dissolved under tongue every 4 hours, or as directed by a licensed practitioner. Children under 4 years: Consult a licensed practitioner.

INACTIVE INGREDIENTS

Sucrose/Lactose